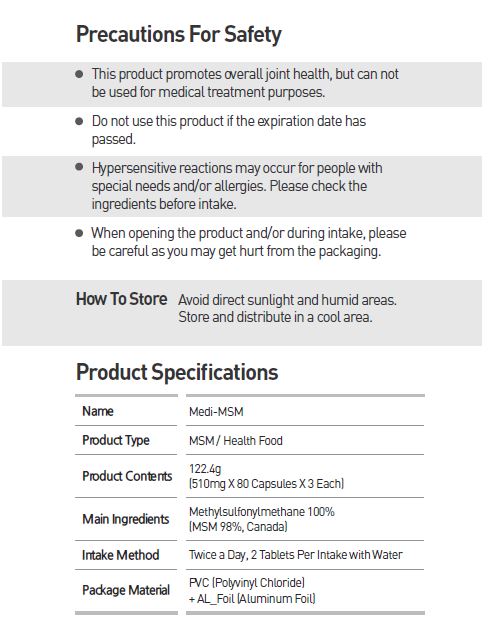 DRUG LABEL: MSM
NDC: 70694-0003 | Form: TABLET
Manufacturer: Inc MBG
Category: otc | Type: HUMAN OTC DRUG LABEL
Date: 20190124

ACTIVE INGREDIENTS: DIMETHYL SULFONE 0.51 g/0.51 g
INACTIVE INGREDIENTS: WATER

INDICATIONS AND USAGE

Twice a Day, 2 Tablets Per Intake with Water

Keep out of reach of children.

DOSAGE AND ADMINISTRATION

for oral use only

Do not use this product if the expiration date has passed

Hypersensitive reactions may occur for people with special needs and/or allergies. Please check the ingredients before intake

When opening the product and/or during intake, please be careful as you may get hurt from the packaging

Avoid direct sunlight and humid areas. Store and distribute in a cool area.

PURPOSE

protect and maintain overall human health

Helps with arthritis, pain relief, inflammation, muscle pain and improves blood flow

INACTIVE INGREDIENT

water

ACTIVE INGREDIENT

Methylsulfonylmethane